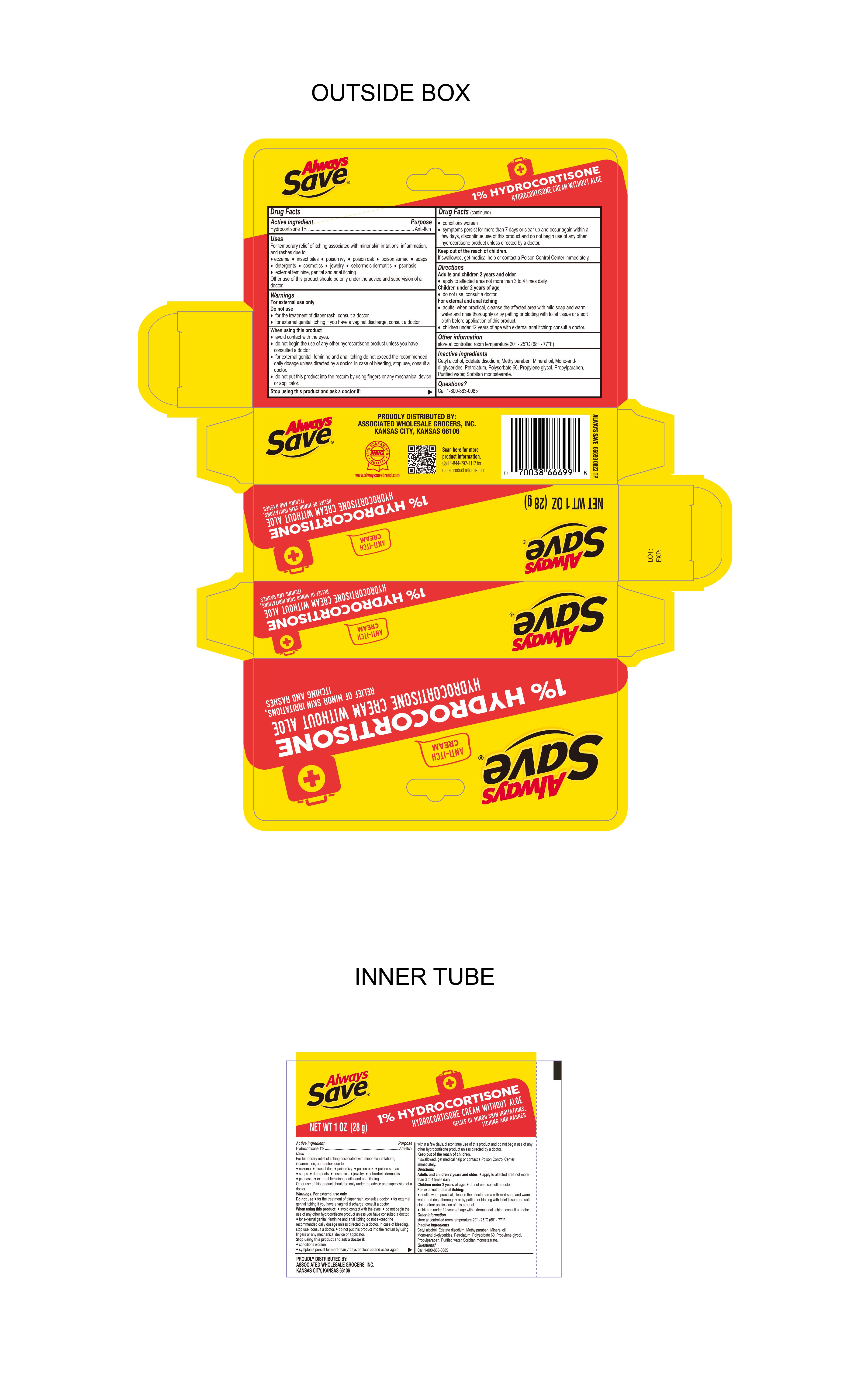 DRUG LABEL: Hydrocortisone Cream
NDC: 69396-147 | Form: CREAM
Manufacturer: Trifecta Pharmaceuticals USA
Category: otc | Type: HUMAN OTC DRUG LABEL
Date: 20240320

ACTIVE INGREDIENTS: HYDROCORTISONE 1 g/100 g
INACTIVE INGREDIENTS: SORBITAN MONOSTEARATE; PROPYLENE GLYCOL; MINERAL OIL; POLYSORBATE 60; PETROLATUM; CETYL ALCOHOL; WATER; PROPYLPARABEN; GLYCERYL MONO AND DIPALMITOSTEARATE; EDETATE DISODIUM; METHYLPARABEN

Always Save Hydrocortisone Cream 1%

Active Ingredient

Hydrocortisone 1%

Purpose

Anti-Itch

Uses

Temporarily relieves itching associated with minor skin irritations, inflammation and rashes due to:

- eczema
- seborrheic dermatitis
- psoriasis
- insect bites
- poison ivy
- poison oak
- poison sumac
- soaps
- detergents
- cosmetics
- jewelry
- external feminine, genital and anal itching

Other uses of this product should be only under the advice and supervision of a doctor

Keep out of reach of children

If swallowed, get medical help or contact a Poison Control Center immediately.

Warnings

- for external use only

Directions

Adults and children 2 years and older

- apply to affected area not more than 3 to 4 times daily

Children under 2 years of age

- do not use, consult a doctor

For external and anal ithcing

- adults: When practical, cleanse the affected area with mild soap and warm water and rinse thoroughly or by patting or blotting with toilet tissue or a soft cloth before application of this product.
- children under 12 years of age with external anal itching, consult a doctor.

Do Not Use

- For the treatment of diaper rash, consult a doctor
- For external genital itching if you have a vaginal discharge, consult a doctor

When using this product

- avoid contact with the eyes
- do not begin the use of any other hydrocortisone product unless you have consulted a doctor
- for external genital, feminine and anal itching do not exceed the recommended daily dosage unless directed by a doctor. In case of bleeding, stop use, consult a doctor.
- Do not put this product into the rectum by using fingersor any mechanical device or applicator.

Stop Using this product and ask a doctor if

- Conditions worsen
- Symptoms persist for more than 7 days or clear up and occur again within a few days, discontinue use of this product and do not begin use of any other hydrocortisone product unless directed by a doctor.

Questions

Call 1-800-883-0085

Inactive Ingredients

Cetyl alcohol, Edetate disodium, methylparaben, mineral oil, mono-and-di-glycerides, petrolatum, polysorbate 60, propylene glycol, propylparaben, purified water, sorbitan monostearate.

Other Information

Store at controlled room temperature 20°C - 25°C (68°F - 77°F).

Other Information

Proudly Distributed By:

Associated Wholesale Grocers, Inc.

Kansas City, Kansas 66106